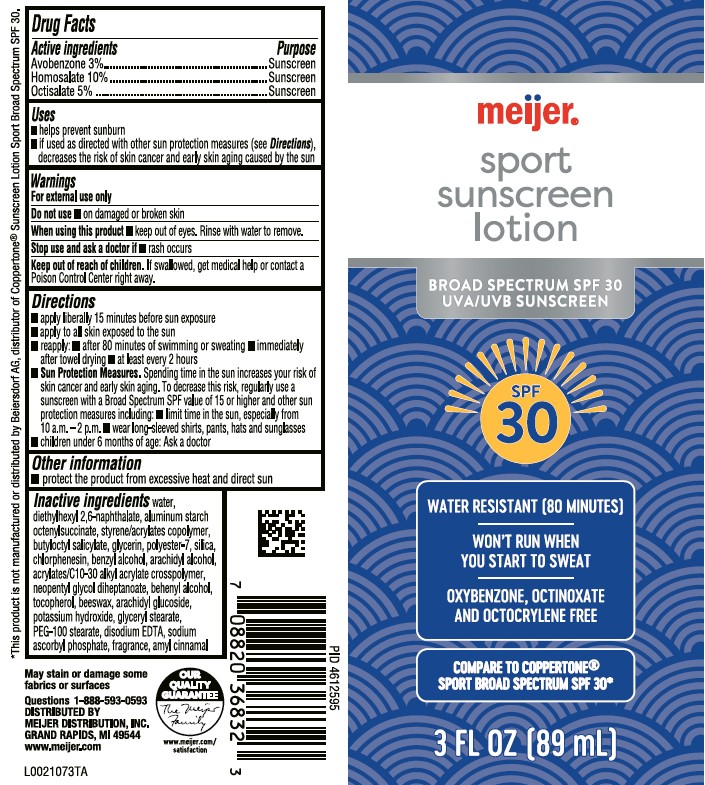 DRUG LABEL: Avobenzone, Homosalate, Octisalate
NDC: 79481-0939 | Form: LOTION
Manufacturer: Meijer, Inc.
Category: otc | Type: HUMAN OTC DRUG LABEL
Date: 20260224

ACTIVE INGREDIENTS: AVOBENZONE 30 mg/1 mL; HOMOSALATE 100 mg/1 mL; OCTISALATE 50 mg/1 mL
INACTIVE INGREDIENTS: WATER; DIETHYLHEXYL 2,6-NAPHTHALATE; ALUMINUM STARCH OCTENYLSUCCINATE; STYRENE/ACRYLAMIDE COPOLYMER (500000 MW); BUTYLOCTYL SALICYLATE; GLYCERIN; POLYESTER-7; SILICON DIOXIDE; CHLORPHENESIN; BENZYL ALCOHOL; ARACHIDYL ALCOHOL; CARBOMER COPOLYMER TYPE B (ALLYL PENTAERYTHRITOL CROSSLINKED); NEOPENTYL GLYCOL DIHEPTANOATE; DOCOSANOL; TOCOPHEROL; YELLOW WAX; ARACHIDYL GLUCOSIDE; POTASSIUM HYDROXIDE; GLYCERYL MONOSTEARATE; PEG-100 STEARATE; EDETATE DISODIUM ANHYDROUS; SODIUM ASCORBYL PHOSPHATE; .ALPHA.-AMYLCINNAMALDEHYDE

Meijer D39.000/D39AA
Sport Sunscreen Lotion SPF 30

Active Ingredients

Avobenzone 3%

Homosalate 10%

Octisalate 5%

Purpose

Sunscreen

Uses

- helps prevent sunburn
- if used as directed with other sun protections measures (see Directions), decreases the risk of skin cancer and early skin aging caused by the sun

Warnings

For external use only

Do not use

- on damaged or broken skin

When using this product

- keep out of eyes. Rinse with water to remove.

Stop use and ask a doctor if

- rash occurs

Keep out of reach of children.

if swallowed, get medical help or contact a Poison Control Center right away.

Directions

- apply liberally 15 minutes before sun exposure
- apply to all skin exposed to the sun
- reapply:
- after 80 minutes of swimming or sweating
- immediately after towel drying
- at least every 2 hours
- Sun Protection Measures. Spending time in the sun increases your risk of skin cancer and early skin aging. To decrease this risk, regularly use a sunscreen with a Broad Spectrum SPF value of 15 or higher and other sun protection measures including:
- limit time in the sun, especially from 10 a.m.–2 p.m.
- wear long-sleeved shirts, pants, hats and sunglasses
- children under 6 months of age: Ask a doctor

Other information

- Protect the product from excessive heat and direct sun

Inactive ingredients

water, diethylhexyl 2,6-naphthalate, aluminum starch octenylsuccinate, styrene/acrylates copolymer, butyloctyl salicylate, glycerin, polyester-7, silica, chlorphenesin, benzyl alcohol, arachidyl alcohol, acrylates/C10-30 alkyl acrylate crosspolymer, neopentyl glycol diheptanoate, behenyl alcohol, tocopherol, beeswax, arachidyl glucoside, potassium hydroxide, glyceryl stearate, PEG-100 stearate, disodium EDTA, sodium ascorbyl phosphate, fragrance, amyl cinnamal

Disclaimer

*This product is not manufactured or distributed by Beiersdorf AG, distributor of Coppertone®Sunscreen Lotion Sport Broad Spectrum SPF 30.

May stain or damage some fabrics or surfaces.

Adverse Reaction

Questions 1-888-593-0593

DISTRIBUTED BY MEIJER DISTRIBUTION, INC.

GRAND RAPIDS, MI 49544

www.meijer.com

OUR QUALITY GUARANTEE

The Meijer Family

www.meijer.com/satisfaction

Principal display panel

meijer®

sport sunscreen lotion

BROAD SPECTRUM SPF 30

UVA/UVB Sunscreen

SPF 30

WATER RESISTANT (80 MINUTES)

WON'T RUN WHEN YOU START TO SWEAT

OXYBENZONE, OCTINOXATE AND OCTOCRYLENE FREE

Compare to Coppertone® Sport Broad Spectrum SPF 30*

3 FL OZ (89 mL)